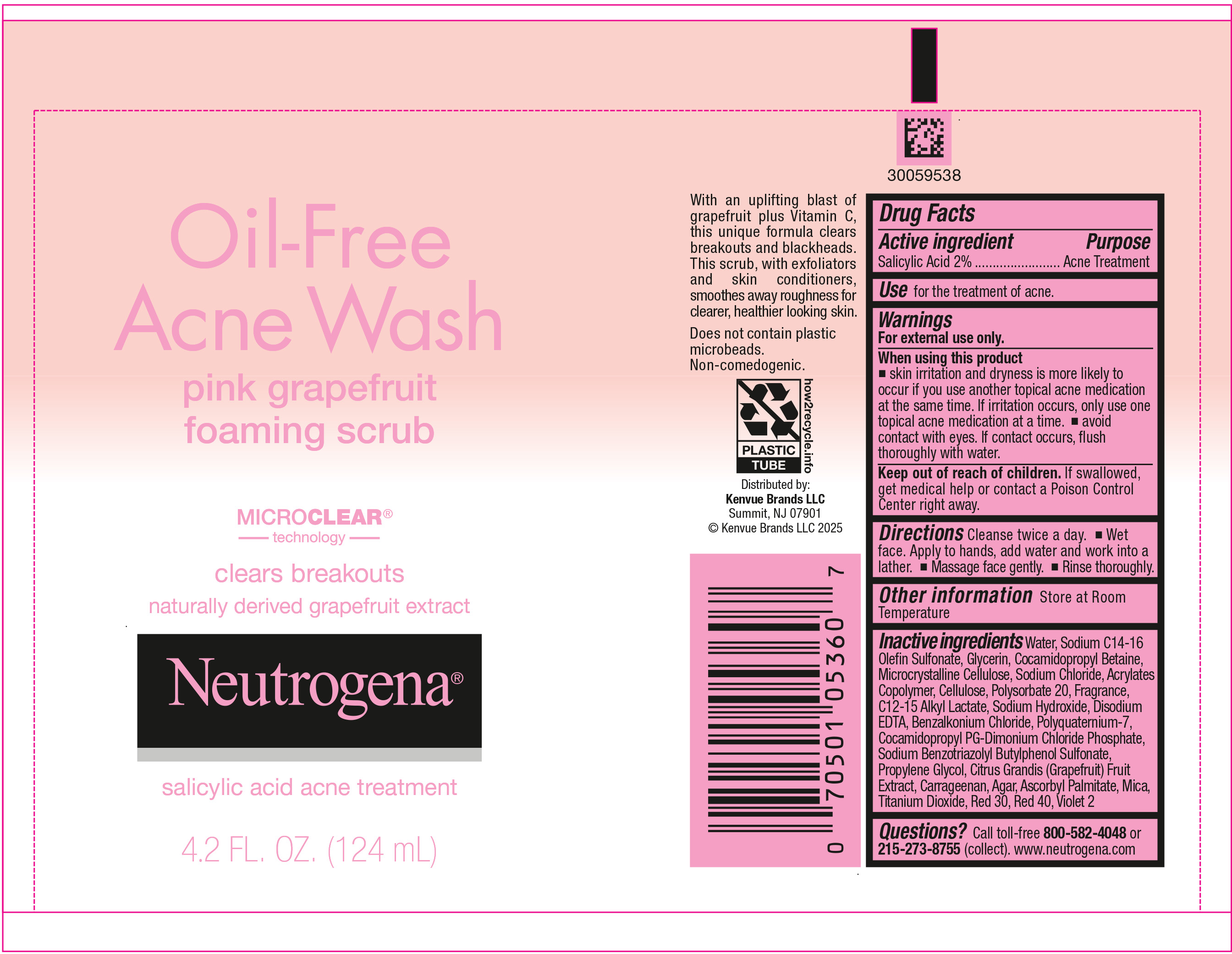 DRUG LABEL: Neutrogena Oil Free Acne Wash Pink Grapefruit Foaming Scrub
NDC: 69968-0610 | Form: GEL
Manufacturer: Kenvue Brands LLC
Category: otc | Type: HUMAN OTC DRUG LABEL
Date: 20250305

ACTIVE INGREDIENTS: SALICYLIC ACID 20 mg/1 mL
INACTIVE INGREDIENTS: MICA; ASCORBYL PALMITATE; TITANIUM DIOXIDE; D&C RED NO. 30; FD&C RED NO. 40; D&C VIOLET NO. 2; WATER; SODIUM C14-16 OLEFIN SULFONATE; GLYCERIN; COCAMIDOPROPYL BETAINE; MICROCRYSTALLINE CELLULOSE; SODIUM CHLORIDE; BUTYL ACRYLATE/METHYL METHACRYLATE/METHACRYLIC ACID COPOLYMER (18000 MW); POWDERED CELLULOSE; POLYSORBATE 20; C12-15 ALKYL LACTATE; SODIUM HYDROXIDE; EDETATE DISODIUM ANHYDROUS; BENZALKONIUM CHLORIDE; POLYQUATERNIUM-7 (70/30 ACRYLAMIDE/DADMAC; 1600000 MW); COCAMIDOPROPYL PROPYLENE GLYCOL-DIMONIUM CHLORIDE PHOSPHATE; SODIUM BENZOTRIAZOLYL BUTYLPHENOL SULFONATE; PROPYLENE GLYCOL; PUMMELO; CARRAGEENAN; AGAR, UNSPECIFIED

Neutrogena® Oil-Free Acne Wash pink grapefruit foaming scrub

Drug Facts

Active ingredients

Salicylic Acid 2%

Purpose

Acne treatment

Use

for the treatment of acne.

Warnings

For external use only.

When using this product

- skin irritation and dryness is more likely to occur if you use another topical acne medication at the same time. If irritation occurs, only use one topical acne medication at a time.
- avoid contact with eyes. If contact occurs, flush thoroughly with water.

Keep out of reach of children. If swallowed, get medical help or contact a Poison Control Center right away.

Directions

Cleanse twice a day.

- Wet face. Apply to hands, add water and work into a lather.
- Massage face gently.
- Rinse thoroughly.

Other information

Store at Room Temperature

Inactive ingredients

Water, Sodium C14-16 Olefin Sulfonate, Glycerin, Cocamidopropyl Betaine, Microcrystalline Cellulose, Sodium Chloride, Acrylates Copolymer, Cellulose, Polysorbate 20, Fragrance, C12-15 Alkyl Lactate, Sodium Hydroxide, Disodium EDTA, Benzalkonium Chloride, Polyquaternium-7, Cocamidopropyl PG-Dimonium Chloride Phosphate, Sodium Benzotriazolyl Butylphenol Sulfonate, Propylene Glycol, Citrus Grandis (Grapefruit) Fruit Extract, Carrageenan, Agar, Ascorbyl Palmitate, Mica, Titanium Dioxide, Red 30, Red 40, Violet 2

Questions?

Call toll- free 800-582-4048 or 215-273-8755 (collect). www.neutrogena.com

Distributed by:
Kenvue Brands LLC
Summit, NJ 07901

PRINCIPAL DISPLAY PANEL - 124 mL Tube Label

Oil-Free

Acne Wash
pink grape fruit
foaming scrub

MICRO CLEAR®
technology

clear breakouts
naturally derived grapefruit extract

Neutrogena®
salicylic acid acne treatment

4.2 FL. OZ. (124 mL)